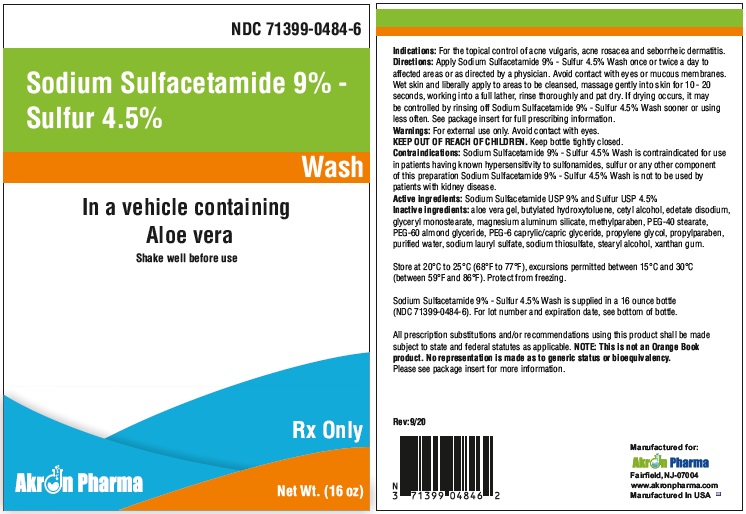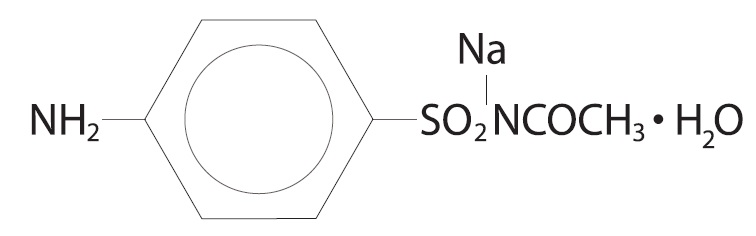 DRUG LABEL: Sodium Sulfacetamide 9% - Sulfur 4.5% Wash
NDC: 71399-0484 | Form: LIQUID
Manufacturer: Akron Pharma Inc.
Category: prescription | Type: HUMAN PRESCRIPTION DRUG LABEL
Date: 20240924

ACTIVE INGREDIENTS: SULFACETAMIDE SODIUM 90 mg/1 g; SULFUR 45 mg/1 g
INACTIVE INGREDIENTS: ALOE VERA LEAF; BUTYLATED HYDROXYTOLUENE; CETYL ALCOHOL; EDETATE DISODIUM; GLYCERYL MONOSTEARATE; MAGNESIUM ALUMINUM SILICATE; PEG-40 STEARATE; PEG-60 ALMOND GLYCERIDES; PEG-6 CAPRYLIC/CAPRIC GLYCERIDES; METHYLPARABEN; PROPYLPARABEN; PROPYLENE GLYCOL; WATER; SODIUM LAURYL SULFATE; SODIUM THIOSULFATE; STEARYL ALCOHOL; XANTHAN GUM

Sodium Sulfacetamide 9% - Sulfur 4.5% Wash
In a vehicle containing Aloe vera
Shake well before use

Rx Only

DESCRIPTION

Sodium sulfacetamide is a sulfonamide with antibacterial activity while sulfur acts as a keratolytic agent. Chemically sodium sulfacetamide is N-[(4-aminophenyl) sulfonyl]-acetamide, monosodium salt, monohydrate. The structural formula is:

Each gram of Sodium Sulfacetamide 9% - Sulfur 4.5% Wash contains 90 mg of Sodium Sulfacetamide and 45 mg of Sulfur in a formulation containing: aloe vera gel, butylated hydroxytoluene, cetyl alcohol, edetate disodium glyceryl monostearate,magnesium aluminum silicate, PEG-40 stearate,PEG-60 almond glyceride, PEG -6 caprylic/capric glyceride, methyl paraben, propyl paraben, propylene glycol, purified water, sodium lauryl sulfate, sodium thiosulfate, stearyl alcohol, xanthan gum.

CLINICAL PHARMACOLOGY

The most widely accepted mechanism of action of sulfonamides is the Woods-Fildes theory, which is based on the fact that sulfonamides act as competitive antagonists to para-aminobenzoic acid (PABA), an essential component for bacterial growth. While absorption through intact skin has not been determined, sodium sulfacetamide is readily absorbed from the gastrointestinal tract when taken orally and excreted in the urine, largely unchanged. The biological half-life has variously been reported as 7 to 12.8 hours. The exact mode of action of sulfur in the treatment of acne is not known, but it has been reported that it inhibits the growth of Propionibacterium acnes and the formation of free fatty acids.

INDICATIONS

Sodium Sulfacetamide 9% - Sulfur 4.5% Wash is indicated in the topical control of acne vulgaris, acne rosacea and seborrheic dermatitis.

CONTRAINDICATIONS:

Sodium Sulfacetamide 9% - Sulfur 4.5% Wash is contraindicated for use by patients having known hypersensitivity to sulfonamides, sulfur or ony other component of this preparation. Sodium Sulfacetamide 9% - Sulfur 4.5% Wash is not to be used by patients with kidney disease.

WARNINGS

Although rare, sensitivity to sodium sulfacetaminde may occur. Therefore, caution and careful supervision should be observed when prescribing this drug for patients who may be prone to hypersensitivity to topical sulfonamides. Systemic toxic reactions such as agranulocytosis, acute hemolytic anemia, purpura hemorrhagica, drug fever, jaundice and contact dermatitis indicate hypersensitivity to sulfonamides. Particular caution should be employed if areas of denuded or abraded skin are involved.

FOR EXTERNAL USE ONLY. Keep away from eyes. Keep out of reach of children. Keep container tightly closed.

PRECAUTIONS

General - If irritation develops, use of the product should be discontinued and appropriate therapy instituted. Patients should be carefully observed for possible local irritation or sensitization during long-term therapy. The object of this therapy is to achieve desquamation without irritation, but sodium sulfacetamide and sulfur can cause reddening and scaling of the epidermis. These side effects are not unusual in the treatment of acne vulgaris, but patients should be cautioned about the possibility.

Information for patients - Avoid contact with eyes, eyelids, lips and mucous membranes. If accidental contact occurs, rinse with water. If excessive irritation develops, discontinue use and consult your physician.

Carcinogenesis, Mutagenesis and Impairment of Fertility - Long-term studies in animals have not been performed to evaluate carcinogenic potential.

PREGNANCY: Category C. Animal reproduction studies have not been conducted with Sodium Sulfacetamide 9% - Sulfur 4.5% Wash. It is not known whether Sodium Sulfacetamide 9% - Sulfur 4% Wash can cause fetal harm when administered to a pregnant woman or can affect reproduction capacity. Sodium Sulfacetamide 9% - Sulfur 4.5% Wash should be given to a pregnant woman only if clearly needed.

NURSING MOTHERS: It is not known whether sodium sulfacetamide is excreted in the human milk following topical use of Sodium Sulfacetamide 9% - Sulfur 4.5% Wash. However, small amounts of orally administered sulfonamides have been reported to be excreted in human milk. In view of this and because many drugs are excreted in human milk, caution should be exercised when Sodium Sulfacetamide 9% - Sulfur 4.5% Wash is administered to a nursing woman.

PEDIATRIC USE: Safety and effectiveness in children under the age of 12 have not been established.

ADVERSE REACTIONS

Although rare, sodium sulfacetamide may cause local irritation.

DOSAGE AND ADMINISTRATION

Apply Sodium Sulfacetamide 9% - Sulfur 4.5% Wash once or twice daily to affected areas or as directed by your physician. Wet skin and liberally apply to areas to be cleansed. Massage gently into skin for 10-20 seconds, working into a full lather, rinse thoroughly and pat dry. If drying occurs, it may be controlled by rinsing off Sodium Sulfacetamide 9% - Sulfur 4.5% Wash sooner or using less often.

HOW SUPPLIED

Sodium Sulfacetamide 9% - Sulfur 4.5% Wash is available in 16 oz (454 g) bottles, NDC 71399-0484-6.

STORAGE AND HANDLING

Store at 20°C to 25°C (68°F to 77°F), excursions permitted between 15°C and 30°C (between 59°F and 86°F). Brief exposure to temperatures up to 40°C (104°F) may be tolerated provided the mean kinetic temperature does not exceed 25°C (77°F); however, such exposure should be minimized.

Protect from freezing.

KEEP THIS AND ALL MEDICATIONS OUT OF THE REACH OF CHILDREN.

All prescription substitutions using this product shall be made subject to state and federal statutes as applicable. NOTE: this is not an Orange Book product and has not been subjected to FDA therapeutic equivalency or other equivalency testing. No representation is made as to generic status or bioequivalency. Each person recommending a prescription substitution using this product shall make such recommendations based on each such person’s professional opinion and knowledge, upon evaluating the active ingredients, excipients, inactive ingredients and chemical formulation information provided herein.

QUESTIONS?

Please Call 1(877) 225-6999

Manufactured for:
Akron Pharma, Inc.
Fairfield, NJ 07004
Manufactured in U.S.A